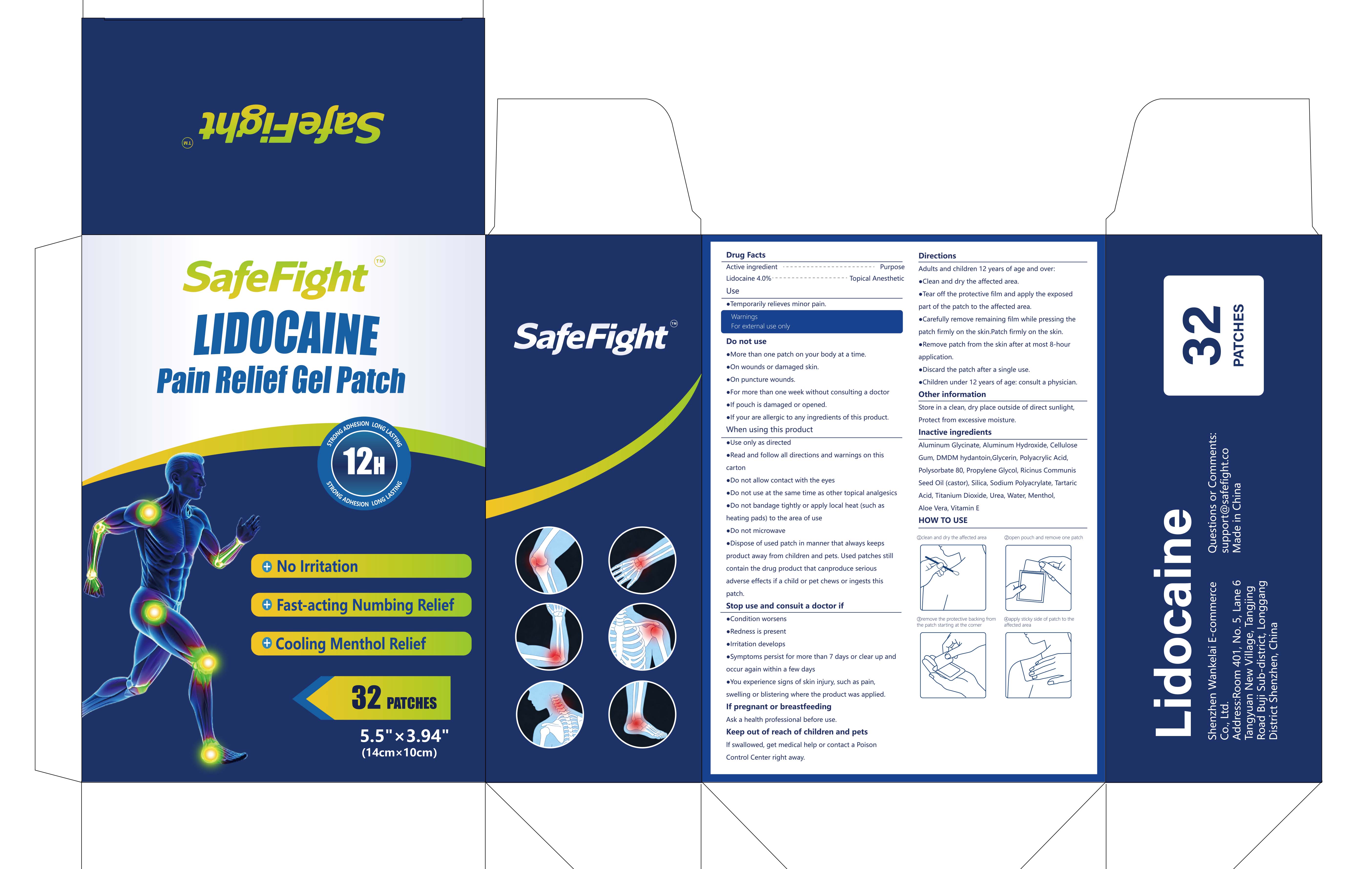 DRUG LABEL: Lidocaine Pain Relief Gel-Patch
NDC: 87413-001 | Form: PATCH
Manufacturer: Shenzhen Wankelai E-commerce Co., Ltd.
Category: otc | Type: HUMAN OTC DRUG LABEL
Date: 20260206

ACTIVE INGREDIENTS: LIDOCAINE 0.04 g/1 1
INACTIVE INGREDIENTS: ALOE VERA LEAF; MENTHOL; ALUMINUM GLYCINATE; CELLULOSE GUM; TARTARIC ACID; ALUMINUM HYDROXIDE; DMDM HYDANTOIN; .ALPHA.-TOCOPHEROL; SILICA; POLYACRYLIC ACID (250000 MW); UREA; GLYCERIN; PROPYLENE GLYCOL; POLYSORBATE 80; WATER; SODIUM POLYACRYLATE (2500000 MW); TITANIUM DIOXIDE; RICINUS COMMUNIS (CASTOR) SEED OIL

87413-001 Lidocaine Pain Relief Gel-Patch

ACTIVE INGREDIENT

Lidocaine 4%

PURPOSE

Topical Anesthetic

INDICATIONS AND USAGE

Temporarily relieves minor pain.

WARNINGS

For external use only

DO NOT USE

More than one patch on your body at a time.
On wounds or damaged skin.
On puncture wounds.
For more than one week without consulting a doctore
lf pouch is damaged or opened.
lf your are allergic to any ingredients of this product.

WHEN USING

Use only as directede
Read and follow all directions and warnings on this carton
Do not allow contact with the eyes
Do not use at the same time as other topical analgesicse
Do not bandage tightly or apply local heat (such asheating pads) to the area of use
Do not microwave
Dispose of used patch in manner that always keeps product away from children and pets. Used patches still contain the drug product that canproduce serious adverse effects if a child or pet chews or ingests this patch.

STOP USE

Condition worsens
Redness is present
lrritation develops
Symptoms persist for more than 7 days or clear up andoccur again within a few days
You experience signs of skin injury, such as pain,swelling or blistering where the product was applied.
Ask a health professional before use.

KEEP OUT OF REACH OF CHILDREN

If swallowed, get medical help or contact a Poison
Control Center right away.

DOSAGE AND ADMINISTRATION

Adults and children 12 years of age and over:
Clean and dry the affected area.
Tear off the protective film and apply the exposed part of the patch to the affected area.
Carefully remove remaining film while pressing the patch firmly on the skin.Patch firmly on the skin.
Remove patch from the skin after at most 8-hour application.
Discard the patch after a single use.
Children under 12 years of age: consult a physician.

INACTIVE INGREDIENT

Aluminum Glycinate, Aluminum Hydroxide, Cellulose Gum
DMDM hydantoin,Glycerin, Polyacrylic Acid
Polysorbate 80, Propylene Glycol, Ricinus Communis Seed Oil (castor)
Silica, Sodium Polyacrylate, Tartaric Acid, Titanium Dioxide, Urea, Water, Menthol
Aloe Vera, Vitamin E